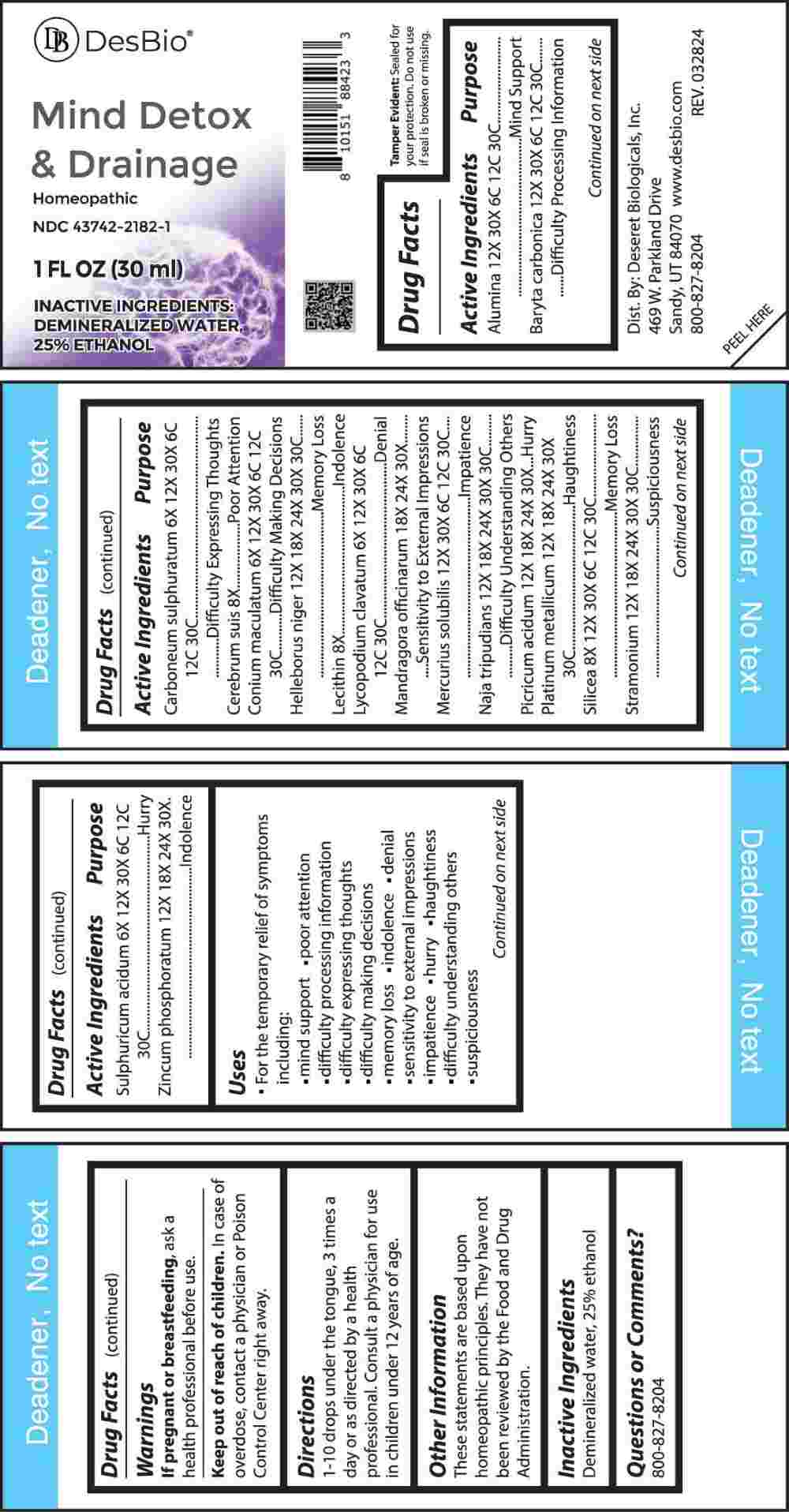 DRUG LABEL: Mind Detox and Drainage
NDC: 43742-2182 | Form: LIQUID
Manufacturer: Deseret Biologicals, Inc.
Category: homeopathic | Type: HUMAN OTC DRUG LABEL
Date: 20240801

ACTIVE INGREDIENTS: ALUMINUM OXIDE 12 [hp_X]/1 mL; BARIUM CARBONATE 12 [hp_X]/1 mL; CARBON DISULFIDE 6 [hp_X]/1 mL; SUS SCROFA CEREBRUM 8 [hp_X]/1 mL; CONIUM MACULATUM FLOWERING TOP 6 [hp_X]/1 mL; HELLEBORUS NIGER ROOT 12 [hp_X]/1 mL; EGG PHOSPHOLIPIDS 8 [hp_X]/1 mL; LYCOPODIUM CLAVATUM SPORE 6 [hp_X]/1 mL; MANDRAGORA OFFICINARUM ROOT 18 [hp_X]/1 mL; MERCURIUS SOLUBILIS 12 [hp_X]/1 mL; NAJA NAJA VENOM 12 [hp_X]/1 mL; PICRIC ACID 12 [hp_X]/1 mL; PLATINUM 12 [hp_X]/1 mL; SILICON DIOXIDE 8 [hp_X]/1 mL; DATURA STRAMONIUM 12 [hp_X]/1 mL; SULFURIC ACID 6 [hp_X]/1 mL; ZINC PHOSPHIDE 12 [hp_X]/1 mL
INACTIVE INGREDIENTS: WATER; ALCOHOL

DRUG FACTS:

ACTIVE INGREDIENTS:

Alumina 12X, 30X, 6C, 12C, 30C, Baryta Carbonica 12X, 30X, 6C, 12C, 30C, Carboneum Sulphuratum 6X, 12X, 30X, 6C, 12C, 30C, Cerebrum Suis 8X, Conium Maculatum 6X, 12X, 30X, 6C, 12C, 30C, Helleborus Niger 12X, 18X, 24X, 30X, 30C, Lecithin 8X, Lycopodium Clavatum 6X, 12X, 30X, 6C, 12C, 30C, Mandragora Officinarum 18X, 24X, 30X, Mercurius Solubilis 12X, 30X, 6C, 12C, 30C, Naja Tripudians 12X, 18X, 24X, 30X, 30C, Picricum Acidum 12X, 18X, 24X, 30X, Platinum Metallicum 12X, 18X, 24X, 30X, 30C, Silicea 8X, 12X, 30X, 6C, 12C, 30C, Stramonium 12X, 18X, 24X, 30X, 30C, Sulphuricum Acidum 6X, 12X, 30X, 6C, 12C, 30C, Zincum Phosphoratum 12X, 18X, 24X, 30X.

PURPOSE:

Alumina – Mind Support, Baryta Carbonica – Difficulty Processing Information, Carboneum Sulphuratum – Difficulty Expressing Thoughts, Cerebrum Suis – Poor Attention, Conium Maculatum – Difficulty Making Decisions, Helleborus Niger – Memory Loss, Lecithin - Indolence, Lycopodium Clavatum - Denial, Mandragora Officinarum – Sensitivity to External Impressions, Mercurius Solubilis - Impatience, Naja Tripudians – Difficulty Understanding Others, Picricum Acidum - Hurry, Platinum Metallicum - Haughtiness, Silicea – Memory Loss, Stramonium - Suspiciousness, Sulphuricum Acidum - Hurry, Zincum Phosphoratum - Indolence

USES:

• For the temporary relief of symptoms including:

• mind support • poor attention • difficulty processing information

• difficulty expressing thoughts • difficulty making decisions • memory loss

• indolence • denial • sensitivity to external impressions • impatience • hurry

• haughtiness • difficulty understanding others • suspiciousness

These statements are based upon homeopathic principles. They have not been reviewed by the Food and Drug Administration.

WARNINGS:

If pregnant or breast-feeding, ask a health professional before use.

Keep out of reach of children. In case of overdose, contact a physician or Poison Control Center right away.
Tamper Evident: Sealed for your protection. Do not use if seal is broken or missing.

KEEP OUT OF REACH OF CHILDREN:

In case of overdose, contact a physician or Poison Control Center right away.

DIRECTIONS:

1-10 drops under the tongue, 3 times a day or as directed by a health professional. Consult a physician for use in children under 12 years of age.

INACTIVE INGREDIENTS:

Demineralized water, 25% ethanol

QUESTIONS:

Dist. By: Deseret Biologicals, Inc.
469 W. Parkland Drive
Sandy, UT 84070

www.desbio.com

800-827-8204

PACKAGE LABEL DISPLAY:

DesBio

Mind Detox

& Drainage

Homeopathic

NDC 43742-2182-1

1 FL OZ (30 ml)